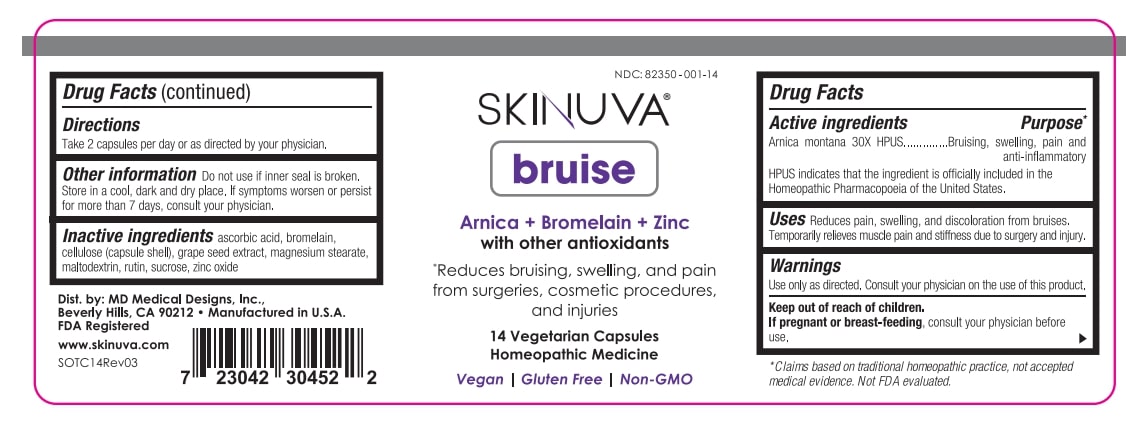 DRUG LABEL: Skinuva Bruise
NDC: 82350-001 | Form: CAPSULE
Manufacturer: MD Medical Designs, Inc.
Category: homeopathic | Type: HUMAN OTC DRUG LABEL
Date: 20260209

ACTIVE INGREDIENTS: ARNICA MONTANA 30 [hp_X]/1 1
INACTIVE INGREDIENTS: SUCROSE; MAGNESIUM STEARATE; MALTODEXTRIN; BROMELAINS; VITIS VINIFERA SEED; ASCORBIC ACID; ZINC OXIDE; POWDERED CELLULOSE; RUTIN

Skinuva Bruise - Labeler Lisitng

Active ingredients Purpose*

Arnica montana 30X HPUS..............Bruising, swelling, pain and

anti-inflammatory

HPUS indicates that the ingredient is officially included in the

Homeopathic Pharmacopoeia of the United States

*Claims based on traditional homeopathic practice, not accepted

medical evidence. Not FDA evaluated.

INDICATIONS AND USAGE

UsesReduces pain, swelling, and discoloration from bruises.

Temporarily relieves muscle pain and stiffness due to surgery and injury.

Warnings

Use only as directed. Consult your physician on the use of this product.

Keep out of reach of children.

If pregnant or breast-feeding, ask a health professional before use.

Keep out of reach of children.

Directions

Take 2 capsules per day or as directed by your physician.

OTHER SAFETY INFORMATION

Other informationDo not use if inner seal is broken.

Store in a cool, dark and dry place. If symptoms worsen or persist

for more than 7 days, consult your physician.

Inactive ingredientsascorbic acid, bromelain,

cellulose (capsule shell), grape seed extract, magnesium stearate,

maltodextrin, rutin, sucrose, zinc oxide

QUESTIONS

Dist. by: MD Medical Designs, Inc.,

Beverly Hills, CA 90212 ● Manufactured in U.S.A.

FDA Registered

www.skinuva.com

SOTC14Rev03

PACKAGE LABEL

SKINUVA

bruise

Arnica + Bromelain + Zinc

with other antioxidatants

*Reduces bruising, swelling, and pain

from surgeries, cosmetic procedures,

and injuries

14 Vegetarian Capsules

Homeopathic Medicine

Vegan | Gluten Free | Non-GMO

PURPOSE

UsesReduces pain, swelling, and discoloration from bruises.

Temporarily relieves muscle pain and stiffness due to surgery and injury